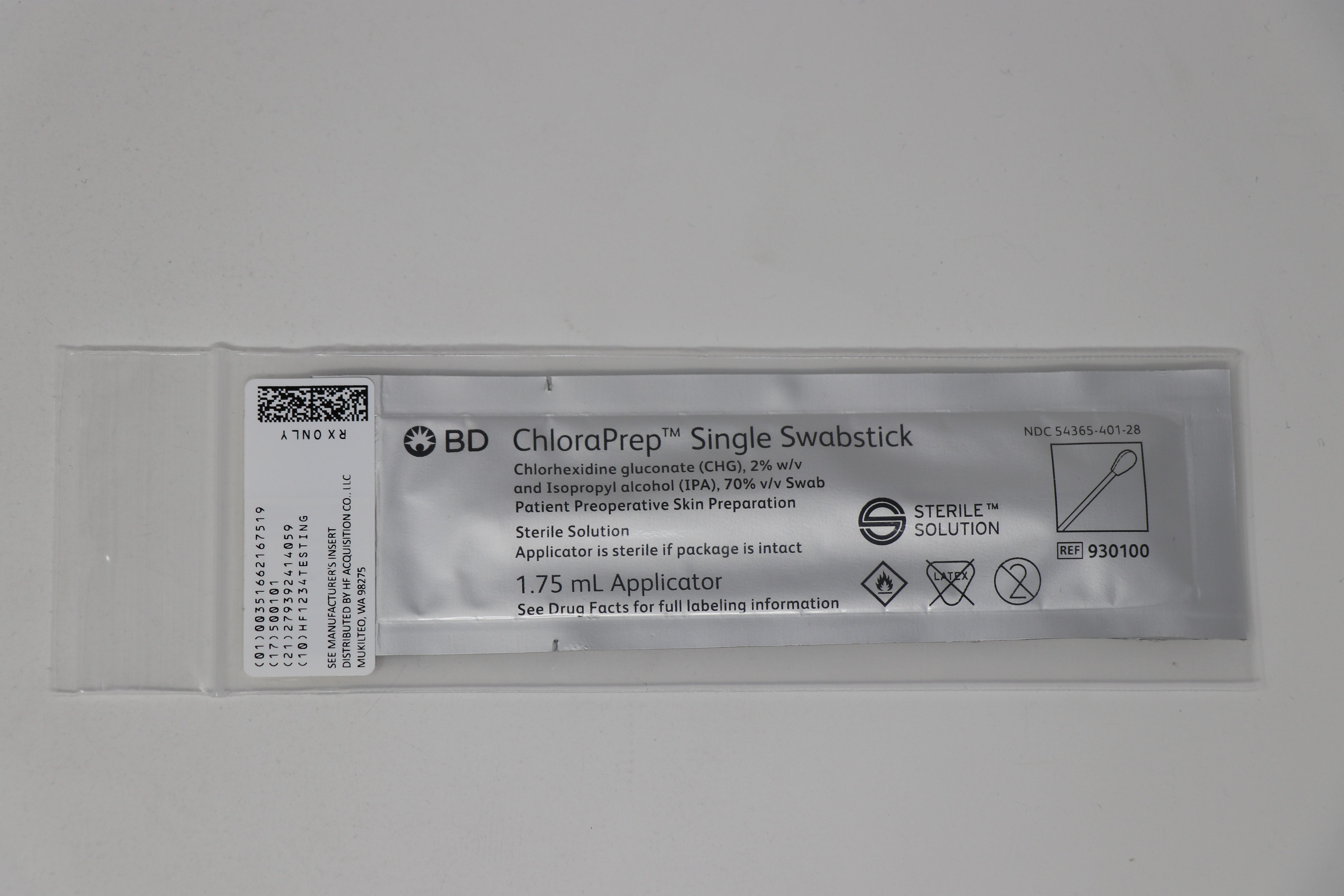 DRUG LABEL: CHLORAPREP
NDC: 51662-1675 | Form: SOLUTION
Manufacturer: HF Acquisition Co LLC, DBA HealthFirst
Category: otc | Type: HUMAN OTC DRUG LABEL
Date: 20251202

ACTIVE INGREDIENTS: ISOPROPYL ALCOHOL 0.7 mL/1 mL; CHLORHEXIDINE GLUCONATE 20 mg/1 mL
INACTIVE INGREDIENTS: WATER

ACTIVE INGREDIENT

Chlorhexidine gluconate (CHG), 2% w/v

and Isopropyl alcohol (IPA), 70% v/v

PURPOSE

Antiseptic

INDICATIONS AND USAGE

for the preparation of the patient's skin prior to surgery. Helps to reduce bacteria that potentially can cause skin infection.

WARNINGS

For external use only. Flammable, keep away from fire or flame.

do not use with electrocautery procedures

Allegery Alert

This product may cause a severe allergic reaction.

Symptoms may include:

wheezing/difficulty breathing
shock
facial swelling
hives
rash

If an allergic reaction occurs, stop use and seek medical help right away.

DO NOT USE

on patients allergic to chlorhexidine gluconate or any other ingredient in this product
for lumbar puncture or in contact with the meninges
on open skin wounds or as a general skin cleanser

WHEN USING

keep out of eyes, ears, and mouth. May cause serious or permanent injury if permitted to enter and remain. If contact occurs, rinse with cold water right away and contact a doctor.

STOP USE

irritation, sensitization, or allergic reaction occurs. These may be signs of a serious condition.

ASK DOCTOR

irritation, sensitization, or allergic reaction occurs. These may be signs of a serious condition.

KEEP OUT OF REACH OF CHILDREN

If swallowed, get medical help or contact a Poison Control Center right away.

DOSAGE AND ADMINISTRATION

use with care in premature infants or infants under 2 months of age. These products may cause irritation or chemical burns.
maximal treatment area for one applicator
one single swabstick applicator is approximately 2.5 in. x 2.5 in. (42 cm 2)
tear pouch at side notch to reveal applicator handles. Do not touch foam applicator tip. Place foam flat side down on the treatment area.
completely wet the treatment area with antiseptic
dry surgical sites (e.g., abdomen or arm): use repeated back-and-forth strokes for 30 seconds. (When using the triple swabstick applicators, use each swabstick sequentially within the 30 seconds). Allow the area to air dry for approximately 30 seconds. Do not blot or wipe away.
moist surgical sites (e.g., inguinal fold): use repeated back-and-forth strokes for 2 minutes. (When using the triple swabstick applicators, use each swabstick sequentially within the 2 minutes). Allow the area to air dry for approximately 1 minute. Do not blot or wipe away.
discard the applicator after a single use along with any portion of the solution not required to cover the prep area. It is not necessary to use the entire amount available.

INACTIVE INGREDIENT

USP purified water

OTHER SAFETY INFORMATION

store between 15-30 ºC (59-86 °F)
avoid freezing and excessive heat above 40 ºC (104 °F)